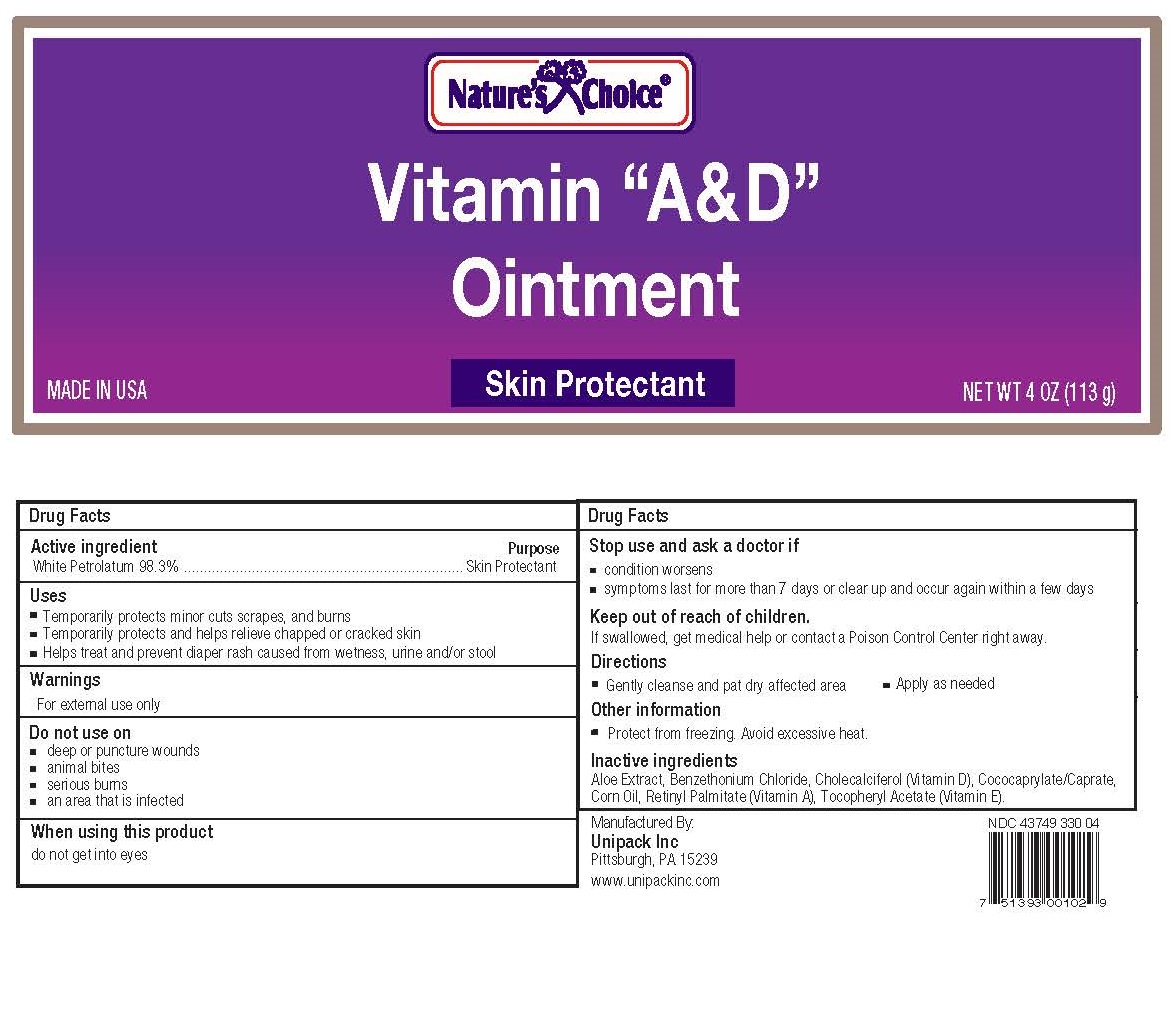 DRUG LABEL: Natures Choice Vitamins A and D
NDC: 43749-330 | Form: OINTMENT
Manufacturer: Unipack LLC
Category: otc | Type: HUMAN OTC DRUG LABEL
Date: 20230118

ACTIVE INGREDIENTS: PETROLATUM 98.3 g/100 g
INACTIVE INGREDIENTS: ALOE VERA LEAF 0.5 g/100 g; VITAMIN A PALMITATE 0.002 g/100 g; CHOLECALCIFEROL 0.001 g/100 g; .ALPHA.-TOCOPHEROL ACETATE, DL- 0.1 g/100 g; COCO-CAPRYLATE/CAPRATE 0.993 1/100 g; BENZETHONIUM CHLORIDE 0.004 1/100 g; CORN OIL 0.1 1/100 g

Natures Choice® Vitamins A and D 4oz

Active Ingredient:

Active Ingredient: Purpose

White Petrolatum USP 98.3%............................................................................Skin Protectant

Inactive ingredients:

aloe extract, benzethonium chloride, cholecalciferol (vitamin D), cococaprylate/caprate, corn oil, retinyl palmitate (vitamin A), tocopheryl acetate (vitamin E)

Purpose

Skin Protectant

Uses

Temporarily protects minor: cuts, scrapes, burns

Temporarily protects and helps relieve chapped or cracked skin

Helps treat and prevent diaper rash caused from wetness, urine, and/or stool.

Warning

For external use only

Do not use on

deep or puncture wounds

animals bites

serious burns

an area that is infected

Stop use and ask a doctor if

condition worsens

symptoms last more than 7 days or clear up and occur again within a few days

Keep out of reach of children

If swallowed, get medical help or contact a Poison Control Center right away

Directions

Gently cleanse and pat dry affected area

Apply as needed

When using this product

do not get into eyes

Other information

Protect from freezing. Avoid excessive heat.